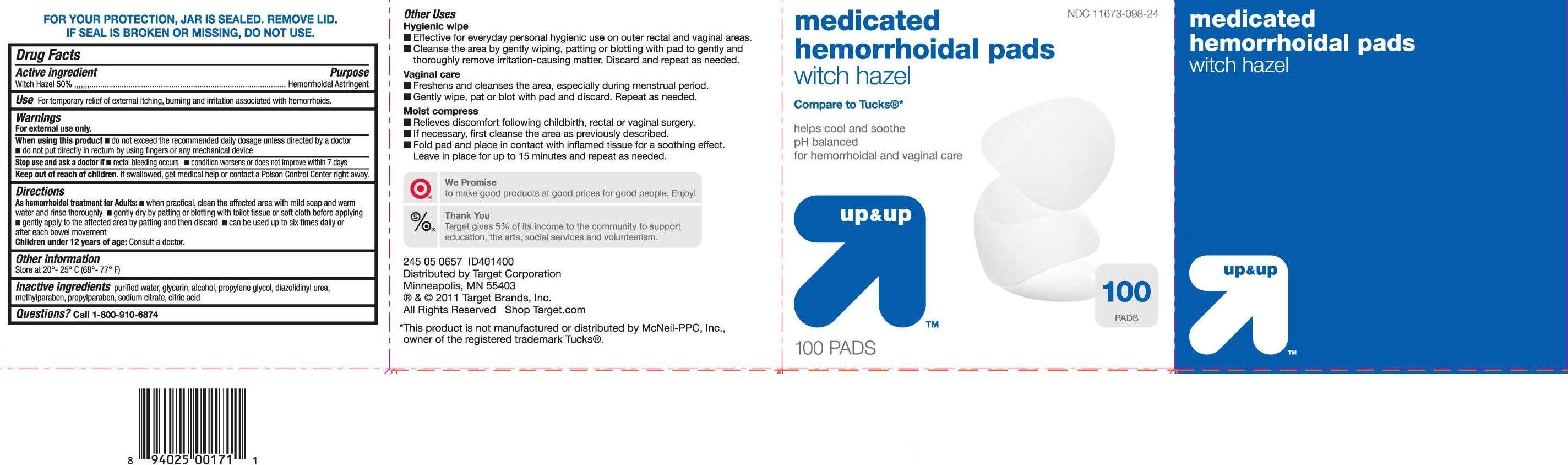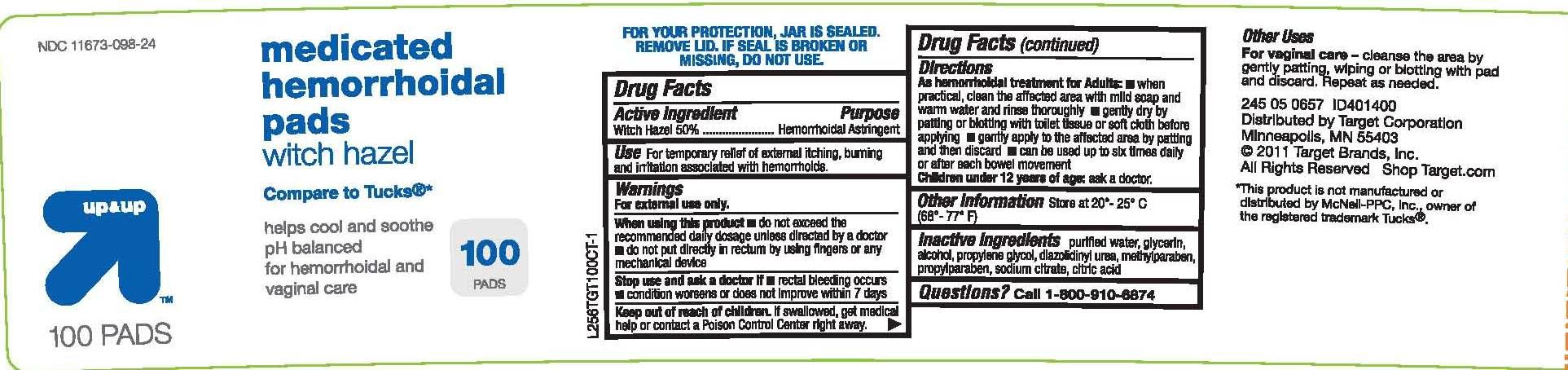 DRUG LABEL: Up and Up Medicated Hemorrhoidal Pads
NDC: 11673-098 | Form: SWAB
Manufacturer: TARGET CORPORATION
Category: otc | Type: HUMAN OTC DRUG LABEL
Date: 20111113

ACTIVE INGREDIENTS: WITCH HAZEL 1 g/1 1
INACTIVE INGREDIENTS: WATER; GLYCERIN; PROPYLENE GLYCOL; CITRIC ACID MONOHYDRATE; DIAZOLIDINYL UREA; METHYLPARABEN; PROPYLPARABEN; SODIUM CITRATE; ALCOHOL

drug facts

Active ingredient Purpose
Witch Hazel 50%.......................................Hemorrhoidal Astringent

Use
- for the temporary relief of external itching, burning and irritation associated with hemorrhoids.

Keep out of reach of children.If swallowed, get medical help or contact a Poison
Control Center right away.

Directions

As hemorrhoidal treatment for adults: when practical, clean the affected area with mild soap and warm water
and rinse thoroughly - gently dry by patting or blotting with toilet tissue or soft cloth before applying - gently
apply to the affected area by patting and then discard - can be used up to six times daily or after each bowel
movement
Children under 12 years of age: ask a doctor
Other Information
- store at 20 degrees - 25 degrees C (68 degrees - 77 degrees F)

Warnings
For external use only.
When using this product
- do not exceed the recommended daily dosage unless directed by a doctor
- do not put directly in rectum by using fingers or any mechanical device
Stop use and ask a doctor if - rectal bleeding occurs - condition worsens
or does not improve within 7 days
Keep out of reach of children. If swallowed, get medical help or contact a Poison
Control Center right away.

Directions

As hemorrhoidal treatment for adults: when practical, clean the affected area with mild soap and warm water
and rinse thoroughly - gently dry by patting or blotting with toilet tissue or soft cloth before applying - gently
apply to the affected area by patting and then discard - can be used up to six times daily or after each bowel
movement
Children under 12 years of age: ask a doctor
Other Information
- store at 20 degrees - 25 degrees C (68 degrees - 77 degrees F)

INACTIVE INGREDIENT

Inactive Ingredients purified water, glycerin, alcohol, propylene glycol, diazolidinyl urea, methylparaben,
propylparaben, sodium citrate, citric acid.